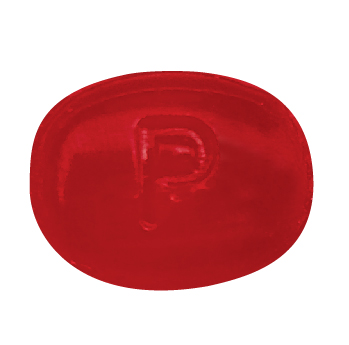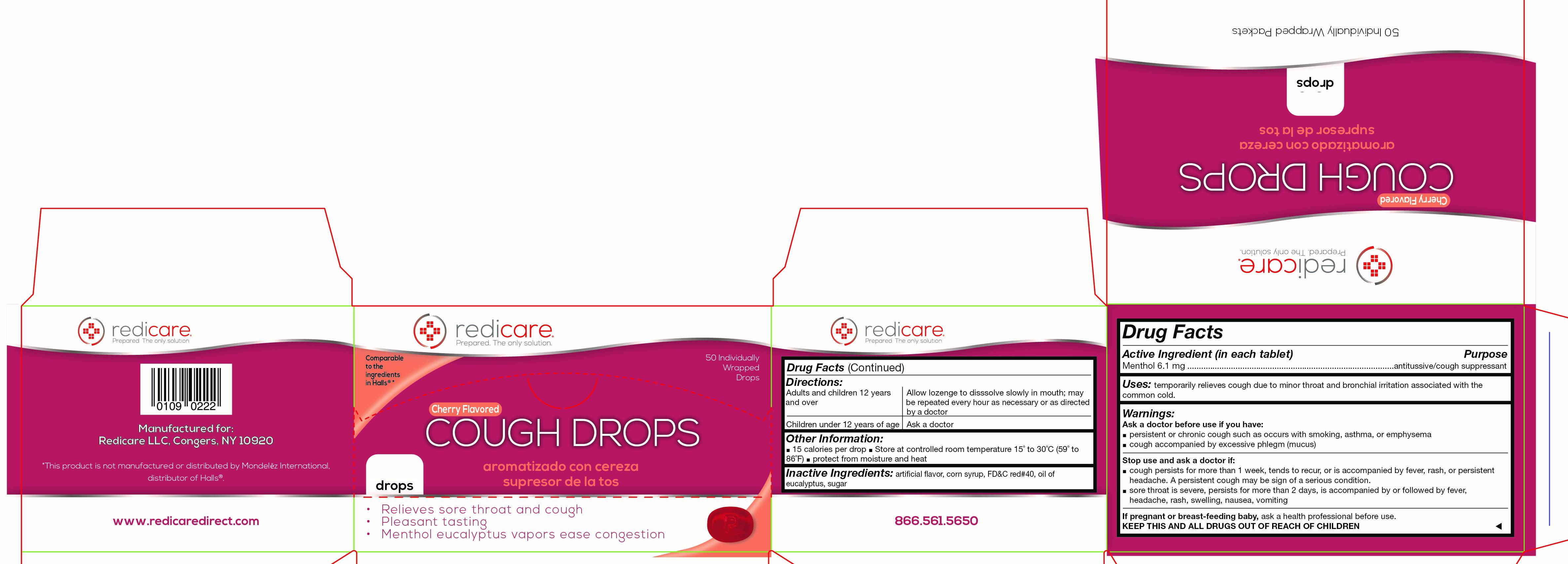 DRUG LABEL: Redicare Cherry Menthol Cough Drops
NDC: 71105-003 | Form: LOZENGE
Manufacturer: Redicare LLC
Category: otc | Type: HUMAN OTC DRUG LABEL
Date: 20210702

ACTIVE INGREDIENTS: MENTHOL 6.1 mg/100 1
INACTIVE INGREDIENTS: EUCALYPTUS OIL; FD&C RED NO. 40; SUCROSE; CORN SYRUP

Cherry Cough Drops

Active Ingredient

Menthol 6.1mg

Purpose

Antitussive (cough suppressant)

Uses:

temporarily relieves a cough due to minor throat and bronchial irritation associated with the common cold.

Ask a doctor before use if you have:

- A persistent or chronic cough such as occurs with smoking, asthma, or emphysema
- cough accompanied by excessive phlegm (mucus)

Stop use and ask a doctor if:

- a cough persists for more than 1 week, tends to recur, or is accompanied by fever, rash or a persistent headache. A persistent cough may be a sign of a serious condition.
- a sore throat is severe, persists for more than 2 days, is accompanied by or followed by fever, headache, rash, swelling, nausea, vomiting.

If pregnant or breastfeeding baby,

ask a health professional before use.

KEEP THIS AND ALL DRUGS

OUT OF REACH OF CHILDREN

Directions

Adults and children 12 years and over: Allow lozenge to dissolve slowly in the mouth; may be repeated every hour as necessary or as directed by a doctor.

Children under 12 years of age: Ask a doctor

Other information

- 15 calories per drop
- Store at controlled room temperature 15 degrees to 30 degrees Celsius (59-86 degrees Fahrenheit)
- protect from moisture and heat

Inactive ingredients

artificial flavor, corn syrup, FD&C red#40, oil of eucalyptus, sugar